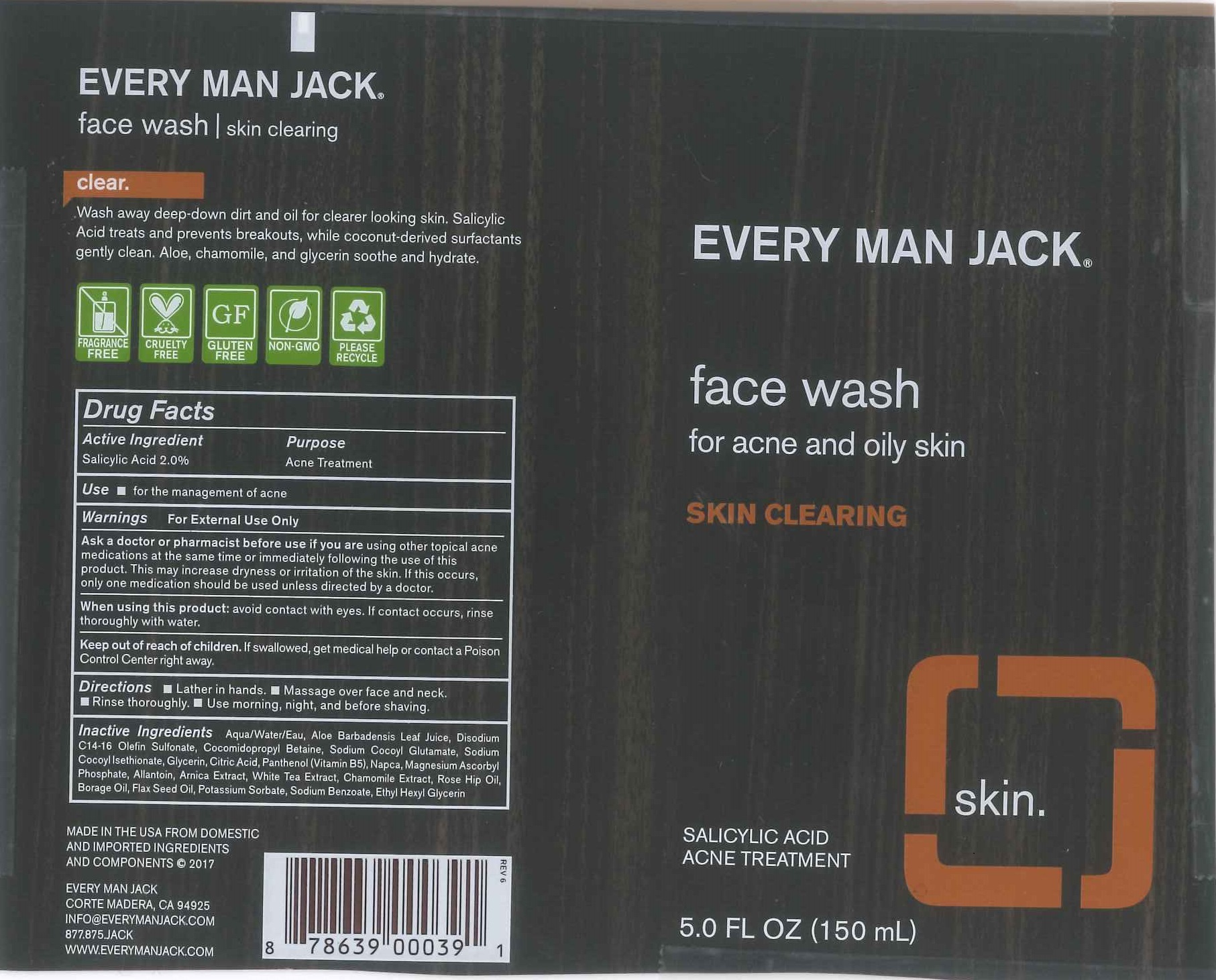 DRUG LABEL: EVERY MAN JACK FACE WASH
NDC: 57934-5013 | Form: CREAM
Manufacturer: EVERY MAN JACK
Category: otc | Type: HUMAN OTC DRUG LABEL
Date: 20211217

ACTIVE INGREDIENTS: SALICYLIC ACID 2 g/100 mL
INACTIVE INGREDIENTS: WATER; ALOE VERA LEAF; SODIUM C14-16 OLEFIN SULFONATE; COCAMIDOPROPYL BETAINE; SODIUM COCOYL GLUTAMATE; SODIUM COCOYL ISETHIONATE; GLYCERIN; ANHYDROUS CITRIC ACID; PANTHENOL; MAGNESIUM ASCORBYL PHOSPHATE; ALLANTOIN; ARNICA MONTANA; TEA LEAF; CHAMOMILE; ROSA MOSCHATA OIL; BORAGE OIL; LINSEED OIL; POTASSIUM SORBATE; SODIUM BENZOATE; ETHYLHEXYLGLYCERIN

EVERY MAN JACK FACE WASH - 57934-5013

ACTIVE INGREDIENT

SALICYLIC ACID 2%

PURPOSE

ACNE TREATMENT

USE

ACNE TREATMENT

WARNINGS

FOR EXTERNAL USE ONLY.

ASK A DOCTOR OR PHARMACIST BEFORE USE IF YOU ARE USING OTHER TOPICAL ACNE MEDICATIONS AT THE SAME TIME OR IMMEDIATELY FOLLOWING THE USE OF THIS PRODUCT. THIS MAY INCREASE DRYNESS OR IRRITATION OF THE SKIN. IF THIS OCCURS, ONLY ONE MEDICATION SHOULD BE USED UNLESS DIRECTED BY A DOCTOR.

WHEN USING THIS PRODUCT: AVOID CONTACT WITH EYES. IF CONTACT OCCURS, RINSE THOROUGHLY WITH WATER.

KEEP OUT OF REACH OF CHILDREN. IF SWALLOWED, GET MEDICAL HELP OR CONTACT A POISON CONTROL CENTER RIGHT AWAY.

DIRECTIONS

- LATHER IN HANDS.
- MASSAGE OVER FACE AND NECK.
- RINSE THOROUGHLY.
- USE MORNING, NIGHT, AND BEFORE SHAVING.

INACTIVE INGREDIENTS

AQUA/WATER.EAU, ALOE BARADENSIS LEAF JUICE, DISODIUM C14-16 OLEFIN SULFONATE, COCOMIDOPROPYL BETAINE, SODIUM COCOYL GLUTAMATE, SODIUM COCOYL iSETHIONATE, GLYCERIN, CITRIC ACID, PANTHENOL (VITAMIN B5), NAPCO, MAGNESIUM ASCORBYL PHOSPHATE, ALLANTOIN, ARNICA EXTRACT, WHITE TEA EXTRACT, CHAMOMILE EXTRACT, ROSE HIP OIL, BORAGE OIL, FLAX SEED OIL, POTASSIUM SORBATE, SODIUM BENZOATE, ETHYL HEXYL GLYCERIN